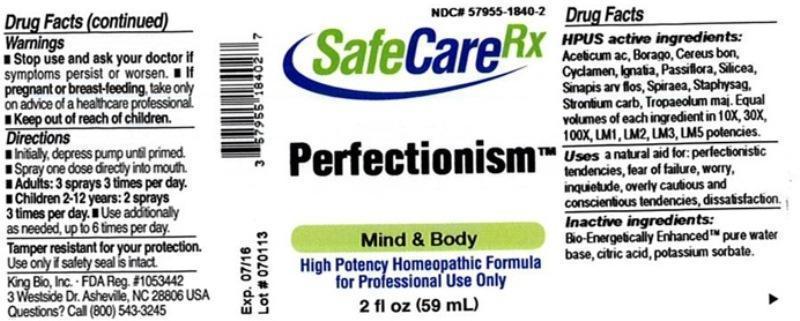 DRUG LABEL: Perfectionism
NDC: 57955-1840 | Form: LIQUID
Manufacturer: King Bio Inc.
Category: homeopathic | Type: HUMAN OTC DRUG LABEL
Date: 20130723

ACTIVE INGREDIENTS: ACETIC ACID 10 [hp_X]/59 mL; BORAGE 10 [hp_X]/59 mL; HARRISIA POMANENSIS STEM 10 [hp_X]/59 mL; CYCLAMEN PURPURASCENS TUBER 10 [hp_X]/59 mL; STRYCHNOS IGNATII SEED 10 [hp_X]/59 mL; PASSIFLORA INCARNATA FLOWERING TOP 10 [hp_X]/59 mL; SILICON DIOXIDE 10 [hp_X]/59 mL; SINAPIS ARVENSIS FLOWERING/FRUITING TOP 10 [hp_X]/59 mL; FILIPENDULA ULMARIA ROOT 10 [hp_X]/59 mL; DELPHINIUM STAPHISAGRIA SEED 10 [hp_X]/59 mL; STRONTIUM CARBONATE 10 [hp_X]/59 mL; TROPAEOLUM MAJUS 10 [hp_X]/59 mL
INACTIVE INGREDIENTS: WATER; CITRIC ACID MONOHYDRATE; POTASSIUM SORBATE

Perfectionism

ACTIVE INGREDIENT

Drug Facts________________________________________________________________________________________________________

HPUS active ingredients: Aceticum acidum, Borago officinalis, Cereus bonplandii, Cyclamen europaeum, Ignatia amara, Passiflora incarnata, Silicea, Sinapis arvensis, flos, Spiraea ulmaria, Staphysagria, Strontium carbonicum, Tropaeolum majus.

Equal volumes of each ingredient in 10X, 30X, 100X, LM1, LM2, LM3, LM5 potencies.

INDICATIONS AND USAGE

Uses a natural aid for: perfectionistic tendencies, fear of failure, worry, inquietude, overly cautious and conscientious tendencies, dissatisfaction.

INACTIVE INGREDIENT

Inactive Ingredients: Bio-Energetically Enhanced™ pure water base, citric acid, potassium sorbate.

Warnings

- Stop use and ask your doctor if symptoms persist or worsen.
- If pregnant or breast-feeding, take only on advice of a healthcare professional.

- Keep out reach of children.

OTHER SAFETY INFORMATION

Tamper resistant for your protection. Use only if safety seal is intact.

Directions

- Initially, depress pump until primed.
- Spray one dose directly into mouth.
- Adults: 3 sprays 3 times per day.
- Children 2-12 years: 2 sprays 3 times per day.
- Use additionally as needed, up to 6 times per day.

PURPOSE

Uses a natural aid for:

- perfectionistic tendencies
- fear of failure
- worry
- inquietude
- overly cautious
- conscientious tendencies
- dissatisfaction